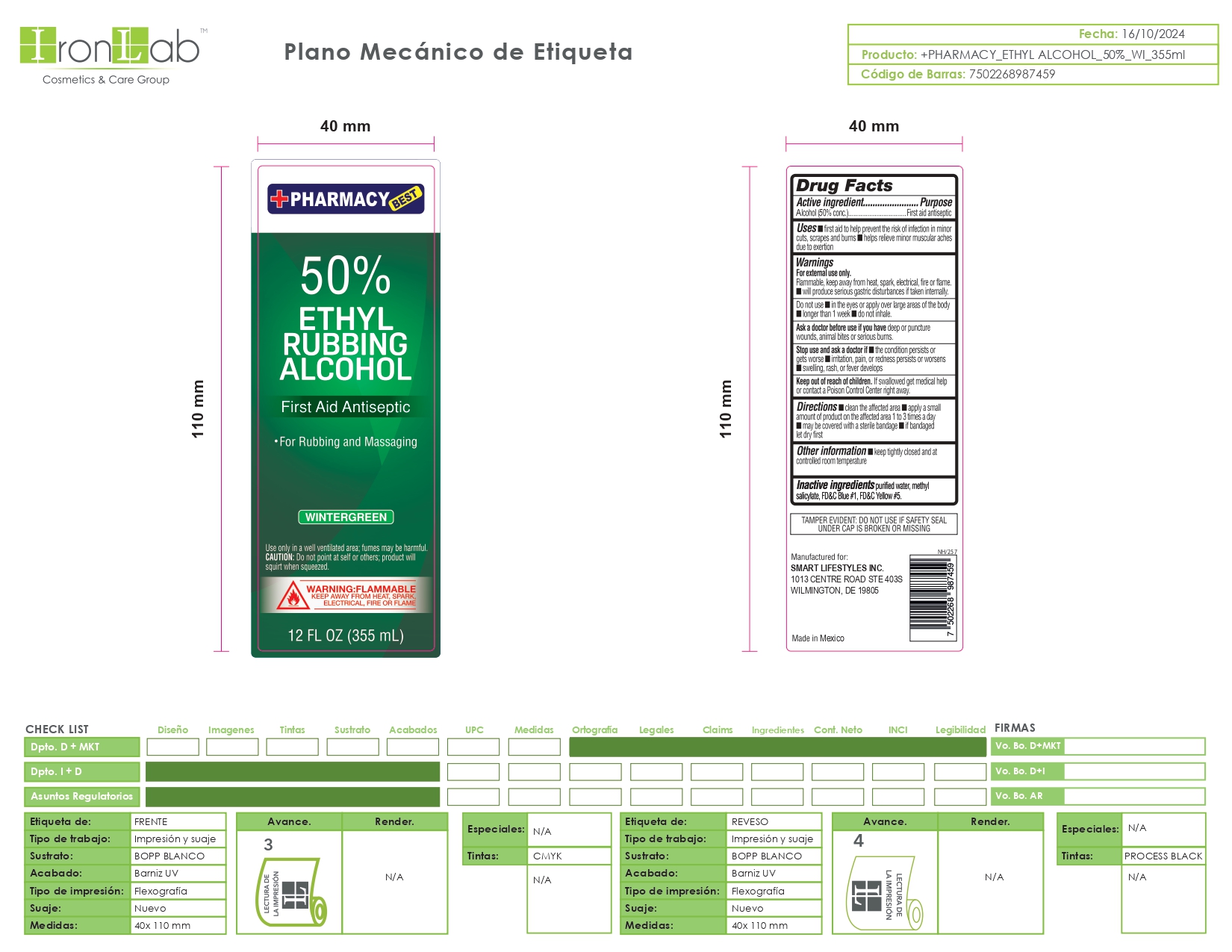 DRUG LABEL: 50 Wintergreen Alcohol
NDC: 74375-040 | Form: LIQUID
Manufacturer: Iron Lab SA de CV
Category: otc | Type: HUMAN OTC DRUG LABEL
Date: 20260217

ACTIVE INGREDIENTS: ALCOHOL 50 mL/100 mL
INACTIVE INGREDIENTS: METHYL SALICYLATE; FD&C BLUE NO. 1; FD&C YELLOW NO. 5; WATER

Wintergreen 50 Hand Sanitizer Iron Lab SA de CV

DOSAGE AND ADMINISTRATION

Thoroughly cover your hands with product and allow to dry without wiping. Children under 6 years of age should be supervised when using this product. Not recommended for infants.

INDICATIONS AND USAGE

Thoroughly cover your hands with product and allow to dry without wiping. Children under 6 years of age should be supervised when using this product. Not recommended for infants.

INACTIVE INGREDIENT

purified water, methyl salicylate, FD&C Blue #1, FD&C Yelloww #5

OTHER SAFETY INFORMATION

Store below 105°F. May discolor some fabrics. Harmful to wood finishes and plastic

KEEP OUT OF REACH OF CHILDREN

If swallowed, get medical help or contact a Poison Control Center right away

ASK DOCTOR

Irritation or redness develops. Condition persist for more than 72 hours.

WARNINGS

For external use only: hands. Flammable, Keep away from fire of flame.

ACTIVE INGREDIENT

50% Ethyl Alcohol

PURPOSE

Antiseptic Alcohol

DO NOT USE

Keep out of eyes. In case of contact with eyes, flush thoroughly with water. Avoid contact with broken skin. Do not inhale or ingest.

PACKAGE LABEL

WinterGreen 50